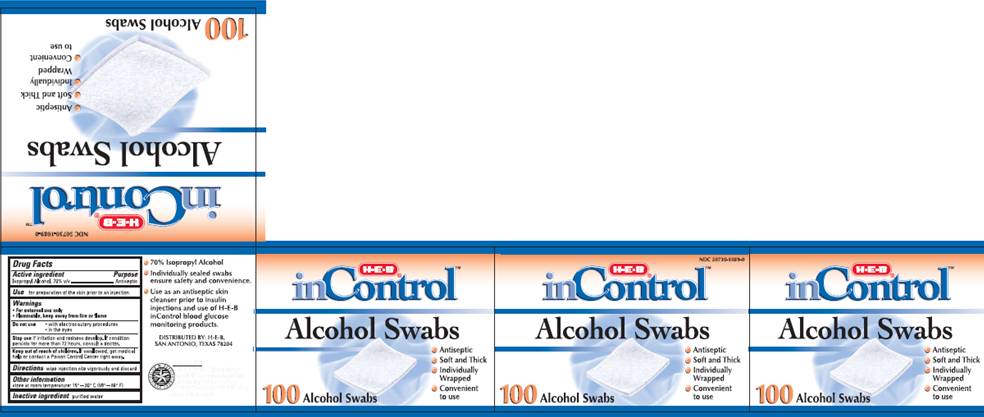 DRUG LABEL: Isopropyl Alcohol Swabs
NDC: 50730-1089 | Form: SWAB
Manufacturer: H and P Industries, Inc. dba Triad Group
Category: otc | Type: HUMAN OTC DRUG LABEL
Date: 20091211

ACTIVE INGREDIENTS: Isopropyl alcohol .7 mL/1 1
INACTIVE INGREDIENTS: water

DRUG FACTS

ACTIVE INGREDIENT

Isopropyl Alcohol 70% v/v

PURPOSE

Antiseptic

USE

For preparation of the skin prior to an injection

WARNINGS

For external use only.
Flammable, keep away from fire or flame.

Do not use

- with electrocautery procedures
- in the eyes

Stop use

if irritation and redness develop. If condition persists for more than 72 hours, consult a doctor.

Keep out of reach of children

If swallowed, get medical help or contact a Poison Control Center right away.

DIRECTIONS

Wipe injection site vigorously and discard

OTHER INFORMATION

Store at room temperature 15° - 30° C (59° - 86° F)

INACTIVE INGREDIENT

purified water

PACKAGE INFORMATION

NDC 50730-1089-0
HEB®
inControl
Alcohol Swabs

- Antiseptic
- Soft and Thick
- Indivdually Wrapped
- Convenient to use

100 Alcohol Swabs

- 70% Isopropyl Alcohol
- Individually sealed swabs ensure safety and convenience.
- Use as an antiseptic skin cleanser prior to insulin injections and use of H-E-B inControl blood glucose monitoring products.

DISTRIBUTED BY: H-E-B
SAN ANTONIO, TEXAS 78204
GUARANTEE
We believe the high quality of this H-E-B product makes it an outstanding value. We hope you'll agree. If not, we'll cheerfully refund your money.